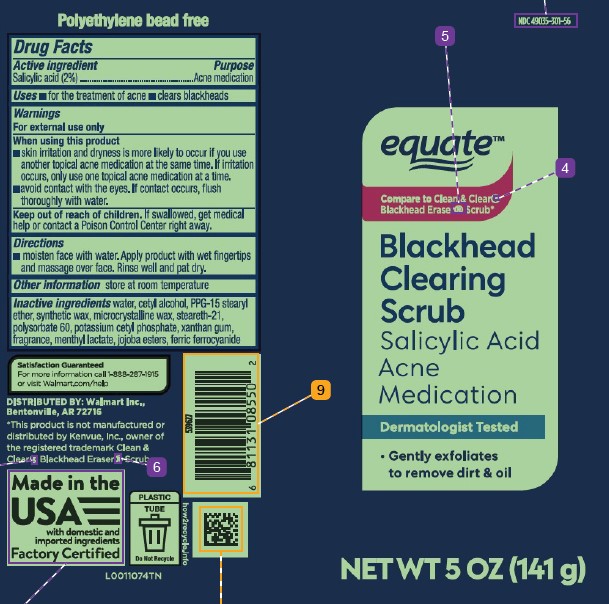 DRUG LABEL: Blackhead Clearing Scrug
NDC: 49035-301 | Form: GEL
Manufacturer: Walmart Inc.
Category: otc | Type: HUMAN OTC DRUG LABEL
Date: 20260227

ACTIVE INGREDIENTS: SALICYLIC ACID 20 mg/1 g
INACTIVE INGREDIENTS: WATER; CETYL ALCOHOL; PPG-15 STEARYL ETHER; SYNTHETIC WAX (1200 MW); MICROCRYSTALLINE WAX; STEARETH-21; POLYSORBATE 60; POTASSIUM CETYL PHOSPHATE; XANTHAN GUM; MENTHYL LACTATE, (-)-; JOJOBA OIL, RANDOMIZED; FERRIC FERROCYANIDE

Equate 219.002/219AC
Blackhead Clearing Scrub

Claim

Polyethylene bead free

Active ingredient

Salicylic acid (2%)

Purpose

Acne medication

Uses

- for the treatment of acne
- clears blackheads

Warnings

For external use only

When using this product

- skin irritation and dryness is more likely to occur if you use another topical acne medication at the same time. If irritation occurs, only use one topical acne medication at a time.
- avoid contact with the eyes. If contact occurs, flush thoroughly with water.

Keep out of reach of children.

If swallowed, get medical help or contact a Poison Control Center right away.

Directions

- moisten face with water. Apply product with wet fingertips and massage over face. Rinse well and pat dry.

Other information

store at room temperature

Inactive ingredients

water, cetyl alcohol, PPG-15 stearyl ether, synthetic wax, microcrystalline wax, steareth-21, polysorbate 60, potassium cetyl phosphate, xanthan gum, fragrance, menthyl lactate, jojoba esters, ferric ferrocyanide

Adverse event

Satisfaction guaranteed

For more information call 1-888-287-1915 or visit Walmart.com/help.

Distributed by: Walmart Inc.,

Bentonville, AR 72716

Made in the USA with domestic and imported ingredients.

Factory Certified

PLASTIC TUBE

Do Not Recycle

how2recycle.info

Disclaimer

*This product is not manufactured or distributed by Kenvue, Inc., owner of the registered trademark Clean & Clear® Blackhead Eraser® Scrub.

Principal display panel

NDC 49035-301-56

equate™

COMPARE TO CLEAN & CLEAR® BLACKHEAD ERASER® SCRUB*

BLACKHEAD CLEARING SCRUB

Salicylic Acid Acne Medication

Dermatologist Tested

- Gently exfoliates to remove dirt & oil

NET WT 5 OZ (141 g)